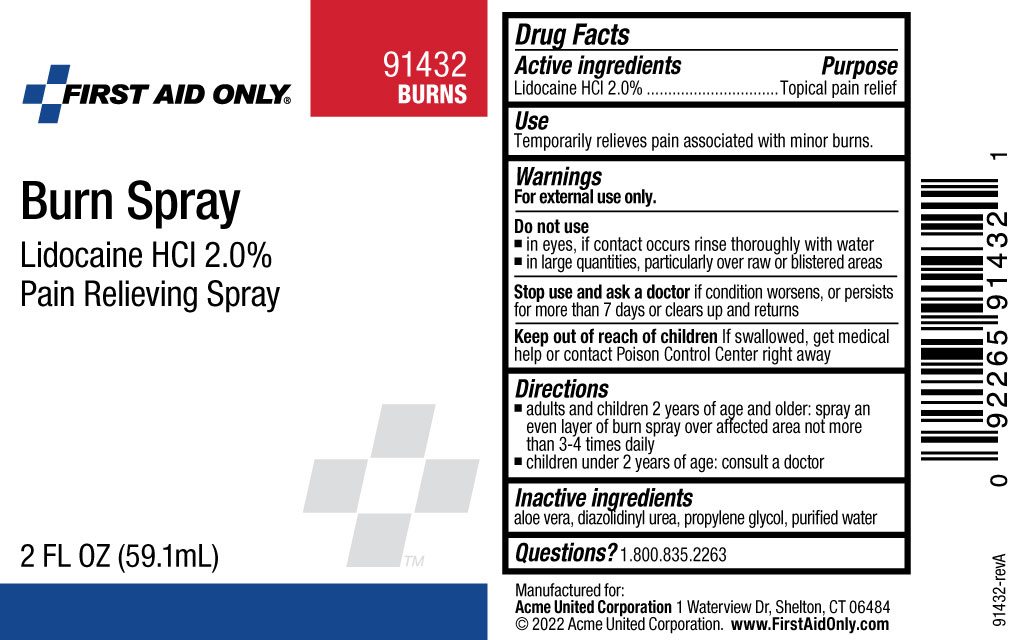 DRUG LABEL: Lidocaine Hydrochloride
NDC: 0924-0934 | Form: LIQUID
Manufacturer: Acme United Corporation
Category: otc | Type: HUMAN OTC DRUG LABEL
Date: 20241112

ACTIVE INGREDIENTS: LIDOCAINE HYDROCHLORIDE 20 mg/1 mL
INACTIVE INGREDIENTS: ALOE VERA LEAF; PROPYLENE GLYCOL; DIAZOLIDINYL UREA; WATER

First Aid Only Burn Spray

Drug Facts

Active ingredients

Lidocaine HCl 2.0%

Purpose

Topical pain relief

Use

Temporarily relieves pain associated with minor burns.

Warnings

For external use only.

Do not use

- in eyes, if contact occurs rinse thoroughly with water
- in large quantities, particularly over raw or blistered areas

Stop use and ask a doctor if condition worsens, or persists for more than 7 days or clears up and returns

- Keep out of reach of children. If swallowed, get medical help or contact Poison Control Center right away

Directions

- adults and children 2 years of age and older: spray an even layer of burn spray over affected area not more than 3-4 times daily
- children under 2 years of age: consult a doctor

Inactive ingredients

aloe vera, diazolidinyl urea, propylene glycol, purified water
----------

Questions? 1.800.835.2263

Bottle Label